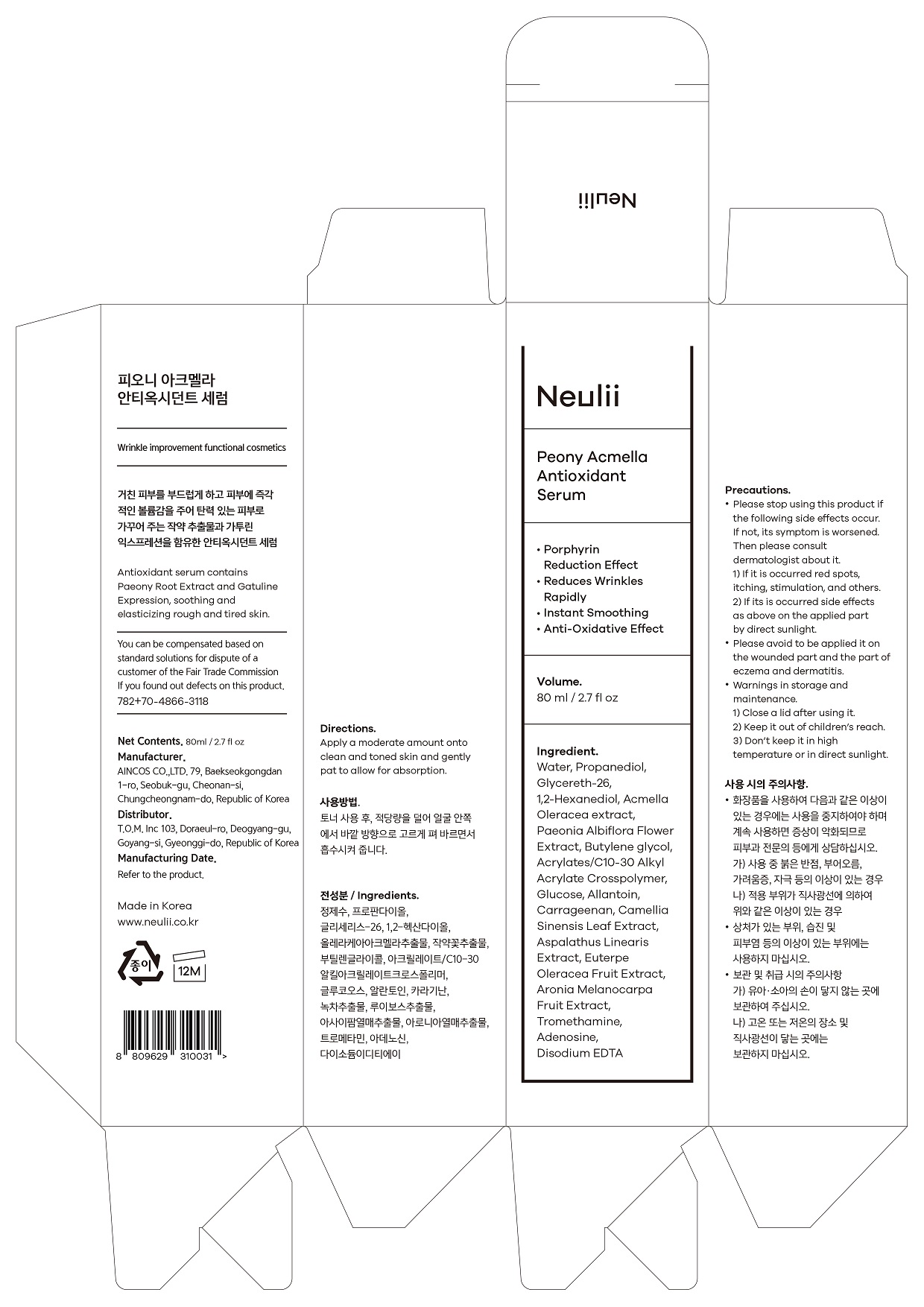 DRUG LABEL: PEONY ACMELLA ANTIOXIDANT SERUM
NDC: 73307-0001 | Form: LIQUID
Manufacturer: TOM Co., Ltd.
Category: otc | Type: HUMAN OTC DRUG LABEL
Date: 20190819

ACTIVE INGREDIENTS: ALLANTOIN 0.1 g/100 mL; ADENOSINE 0.04 g/100 mL
INACTIVE INGREDIENTS: WATER

ACTIVE INGREDIENT

allantoin, adenosine

INACTIVE INGREDIENT

Water
Propanediol
Glycereth-26
1,2-Hexanediol
Acmella Oleracea Extract
Paeonia Albiflora Flower Extract
Butylene glycol
Acrylates/C10-30 Alkyl Acrylate Crosspolymer
Glucose
Carrageenan
Camellia Sinensis Leaf Extract
Aspalathus Linearis Extract
Euterpe Oleracea Fruit Extract
Aronia Melanocarpa Fruit Extract
Tromethamine
Disodium EDTA

PURPOSE

wrinkle improvement functional cosmetic

keep out or reach of the children

INDICATIONS AND USAGE

Apply a moderate amount ontoclean and toned skin and gentlypat to allow for absorption.

WARNINGS

Precautions

Please stop using this product ifthe following side effects occur.If not, its symptom is worsened.

Then please consultdermatologist about it.

1) If it is occurred red spots,itching, stimulation, and others.

2) If it is occurred side effectsas above on the applied partby direct sunlight.

Please avoid to be applied it onthe wounded part and the part ofeczema and dermatitis.

Warnings in storage andmaintenance.

1) Close a lid after using it.

2) Keep it out of children’s reach.

3) Don’t keep it in hightemperature or in direct sunlight.

DOSAGE AND ADMINISTRATION

for external use only